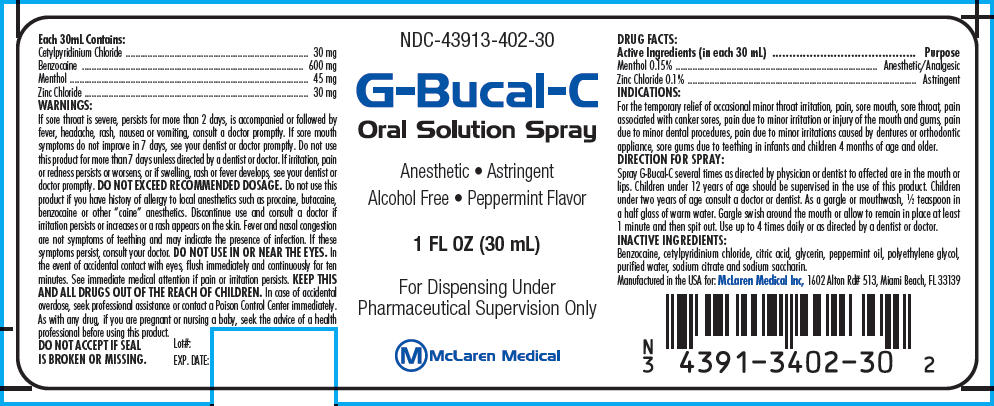 DRUG LABEL: G-BUCAL-C
NDC: 43913-402 | Form: SPRAY
Manufacturer: MCLAREN MEDICAL INC
Category: otc | Type: HUMAN OTC DRUG LABEL
Date: 20150629

ACTIVE INGREDIENTS: MENTHOL, UNSPECIFIED FORM 45 mg/30 mL; ZINC CHLORIDE 30 mg/30 mL
INACTIVE INGREDIENTS: BENZOCAINE; CETYLPYRIDINIUM CHLORIDE; CITRIC ACID MONOHYDRATE; GLYCERIN; PEPPERMINT OIL; POLYETHYLENE GLYCOLS; WATER; SODIUM CITRATE; SACCHARIN SODIUM

G-BUCAL-C

DRUG FACTS

ACTIVE INGREDIENT

Active Ingredients (in each 30 mL) | Purpose
Menthol 0.15% | Anesthetic/Analgesic
Zinc Chloride 0.1% | Astringent

INDICATIONS

For the temporary relief of occasional minor throat irritation, pain, sore mouth, sore throat, pain associated with canker sores, pain due to minor irritation or injury of the mouth and gums, pain due to minor dental procedures, pain due to minor irritations caused by dentures or orthodontic appliance, sore gums due to teething in infants and children 4 months of age and older.

DIRECTION FOR SPRAY

Spray G-Bucal-C several times as directed by physician or dentist to affected are in the mouth or lips. Children under 12 years of age should be supervised in the use of this product. Children under two years of age consult a doctor or dentist. As a gargle or mouthwash, ½ teaspoon in a half glass of warm water. Gargle swish around the mouth or allow to remain in place at least 1 minute and then spit out. Use up to 4 times daily or as directed by a dentist or doctor.

INACTIVE INGREDIENTS

Benzocaine, cetylpyridinium chloride, citric acid, glycerin, peppermint oil, polyethylene glycol, purified water, sodium citrate and sodium saccharin.

Each 30mL Contains:

Cetylpyridinium Chloride | 30 mg
Benzocaine | 600 mg
Menthol | 45 mg
Zinc Chloride | 30 mg

WARNINGS

If sore throat is severe, persists for more than 2 days, is accompanied or followed by fever, headache, rash, nausea or vomiting, consult a doctor promptly. If sore mouth symptoms do not improve in 7 days, see your dentist or doctor promptly. Do not use this product for more than 7 days unless directed by a dentist or doctor. If irritation, pain or redness persists or worsens, or if swelling, rash or fever develops, see your dentist or doctor promptly. DO NOT EXCEED RECOMMENDED DOSAGE. Do not use this product if you have history of allergy to local anesthetics such as procaine, butacaine, benzocaine or other "caine" anesthetics. Discontinue use and consult a doctor if irritation persists or increases or a rash appears on the skin. Fever and nasal congestion are not symptoms of teething and may indicate the presence of infection. If these symptoms persist, consult your doctor. DO NOT USE IN OR NEAR THE EYES. In the event of accidental contact with eyes, flush immediately and continuously for ten minutes. See immediate medical attention if pain or irritation persists.

KEEP OUT OF REACH OF CHILDREN

KEEP THIS AND ALL DRUGS OUT OF THE REACH OF CHILDREN. In case of accidental overdose, seek professional assistance or contact a Poison Control Center immediately. As with any drug, if you are pregnant or nursing a baby, seek the advice of a health professional before using this product.

PRINCIPAL DISPLAY PANEL - 30 mL Bottle Label

NDC-43913-402-30

G-Bucal-C
Oral Solution Spray

Anesthetic • Astringent
Alcohol Free • Peppermint Flavor

1 FL OZ (30 mL)

For Dispensing Under
Pharmaceutical Supervision Only

McLaren Medical